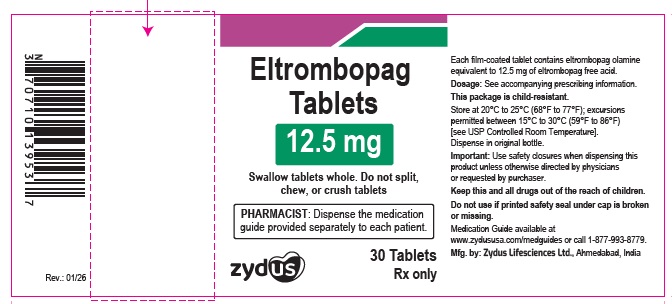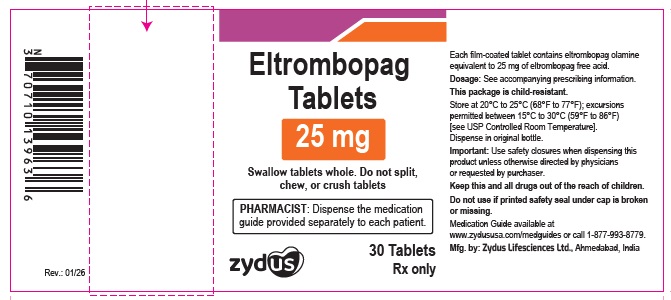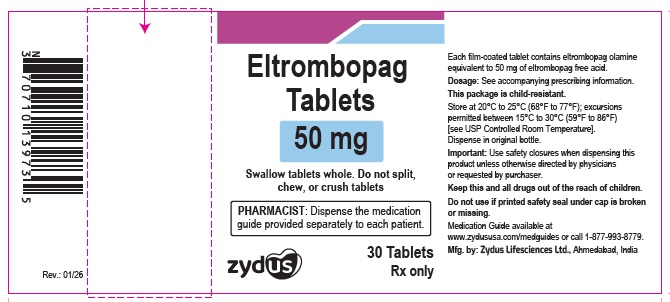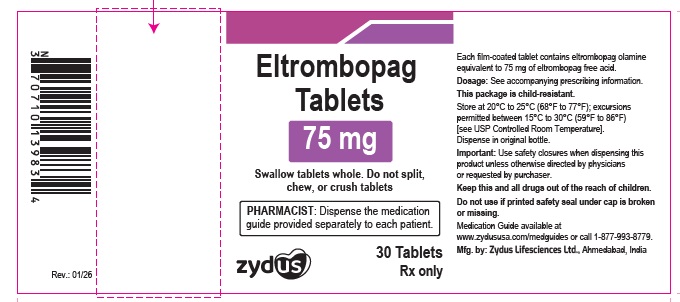 DRUG LABEL: ELTROMBOPAG
NDC: 70771-1925 | Form: TABLET
Manufacturer: Zydus Lifesciences Limited
Category: prescription | Type: HUMAN PRESCRIPTION DRUG LABEL
Date: 20260114

ACTIVE INGREDIENTS: ELTROMBOPAG OLAMINE 12.5 mg/1 1
INACTIVE INGREDIENTS: HYPROMELLOSE 2910 (6 MPA.S); MICROCRYSTALLINE CELLULOSE 101; POLYETHYLENE GLYCOL 400; POVIDONE K30; SODIUM STARCH GLYCOLATE TYPE A POTATO; SODIUM STEARYL FUMARATE; TITANIUM DIOXIDE; XYLITOL

ELTROMBOPAG tablets, for oral use

PACKAGE LABEL.PRINCIPAL DISPLAY PANEL

NDC 70771-1925-3

Eltrombopag Tablets, 12.5 mg

30 Tablets

Rx only

NDC 70771-1926-3

Eltrombopag Tablets, 25 mg

30 Tablets

Rx only

NDC 70771-1927-3

Eltrombopag Tablets, 50 mg

30 Tablets

Rx only

NDC 70771-1928-3

Eltrombopag Tablets, 75 mg

30 Tablets

Rx only